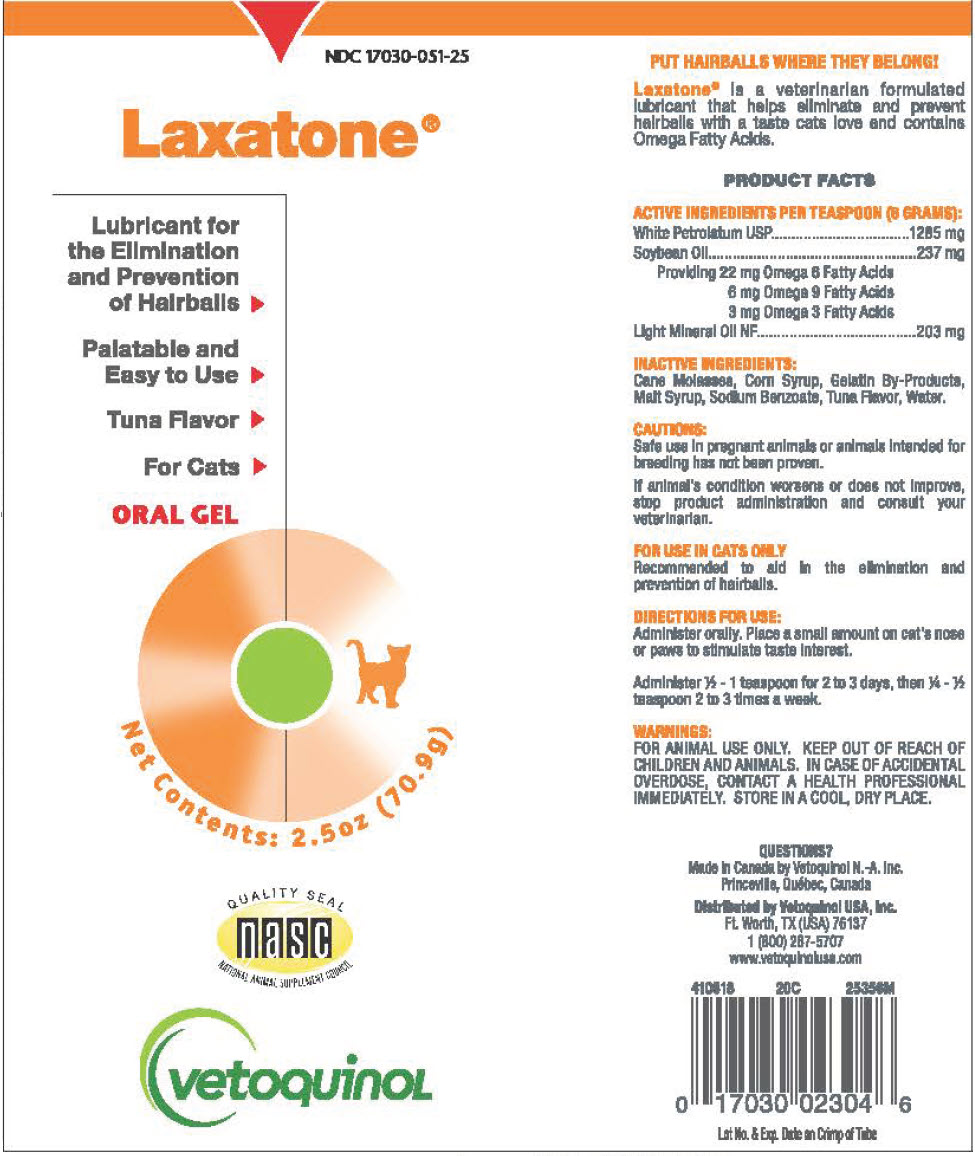 DRUG LABEL: Laxatone Tuna
NDC: 17030-051 | Form: GEL
Manufacturer: Vetoquinol USA, Inc.
Category: animal | Type: OTC ANIMAL DRUG LABEL
Date: 20221130

ACTIVE INGREDIENTS: Petrolatum 214.2 mg/1 g; Mineral Oil 33.8 mg/1 g
INACTIVE INGREDIENTS: Water; Corn Syrup; Soybean Oil; Maltose Syrup; Molasses; GELATIN, UNSPECIFIED; Sodium Benzoate; Tuna, Unspecified

Laxatone® Tuna Flavored

VETERINARY INDICATIONS

PUT HAIRBALLS WHERE THEY BELONG!

Laxatone® is a veterinarian formulated lubricant that helps eliminate and prevent hairballs with a taste cats love and contains Omega Fatty Acids.

PRODUCT FACTS

ACTIVE INGREDIENTS PER TEASPOON (6 GRAMS):

White Petrolatum USP |  | 1285 mg
Soybean Oil |  | 237 mg
Providing 22 mg Omega 6 Fatty Acids 6 mg Omega 9 Fatty Acids 3 mg Omega 3 Fatty Acids
Light Mineral Oil NF |  | 203 mg

INACTIVE INGREDIENTS:

Cane Molasses, Corn Syrup, Gelatin By-Products, Malt Syrup, Sodium Benzoate, Tuna Flavor, Water.

CAUTIONS:

Safe use in pregnant animals or animals intended for breeding has not been proven.

If animal's condition worsens or does not improve, stop product administration and consult your veterinarian.

FOR USE IN CATS ONLY

Recommended to aid in the elimination and prevention of hairballs.

DIRECTIONS FOR USE:

Administer orally. Place a small amount on cat's nose or paws to stimulate taste interest.

Administer ½ - 1 teaspoon for 2 to 3 days, then ¼ - ½ teaspoon 2 to 3 times a week.

WARNINGS:

FOR ANIMAL USE ONLY. KEEP OUT OF REACH OF CHILDREN AND ANIMALS. IN CASE OF ACCIDENTAL OVERDOSE, CONTACT A HEALTH PROFESSIONAL IMMEDIATELY. STORE IN A COOL, DRY PLACE.

QUESTIONS?

Made in Canada by Vetoquinol N.-A. Inc.
Princeville, Québec, Canada

Distributed by Vetoquinol USA, Inc.
Ft. Worth, TX (USA) 76137
1 (800) 267-5707
www.vetoquinolusa.com

Lot No. & Exp. Date on Crimp of Tube

PRINCIPAL DISPLAY PANEL - 70.9 g Tube Label

NDC 17030-051-25

Laxatone®

Lubricant for
the Elimination
and Prevention
of Hairballs ⏵

Palatable and
Easy to Use ⏵

Tuna Flavor ⏵

For Cats ⏵

ORAL GEL

Net Contents: 2.5oz (70.9g)

QUALITY SEAL
nasc
NATIONAL ANIMAL SUPPLEMENT COUNCIL

vetoquinol